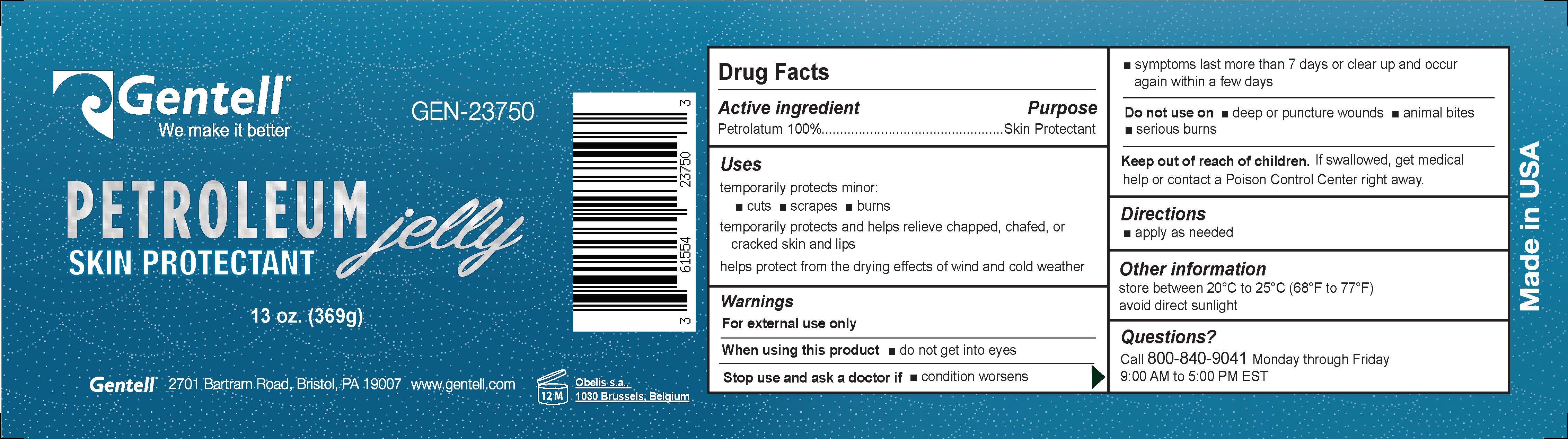 DRUG LABEL: Petroleum Jelly
NDC: 61554-600 | Form: JELLY
Manufacturer: Gentell, Inc.
Category: otc | Type: HUMAN OTC DRUG LABEL
Date: 20240813

ACTIVE INGREDIENTS: PETROLATUM 1 g/1 g

Petroleum Jelly

Active Ingredient

Petrolatum

keep out of reach of children

Purpose

Gentell petroleum Jelly temporarily protects minor cuts, scraped, and burns. It temporarily protects and helps relieve chapped, chafered, or cracked skin and lips, and helps protect from the drying effects of wind and col weather.

Indications & useage

Gentell Petroleum Jelly temporarily protects minor cuts, scrapes, and burns. It temporarily protects and helps relieve chapped, chafed, or cracked skin and lips, and helps protect from the drying effects of wind and cold weather.

Dosage & Administration

Apply as needed

Warnings Section

For external use only

When using this product,do not get into eyes

Stop use and ask a doctor if condition worsens or if symptoms last more than seven days or clear up and occur again within a few days

Do not use on deep or puncture wounds, animal bites or serious burns

Keep out of reach of children

If swallowed, get medical help or contact a Poison control Center right away

Inactive Ingredients

There are no inactive ingredients

Petroleum Jelly

Gentell

Petroleum Jelly

Skin Protectant

GEN-23750 13oz.(369g)

Gentell 2701 Bartram Road, Bristol, PA 19007 www.gentell.com